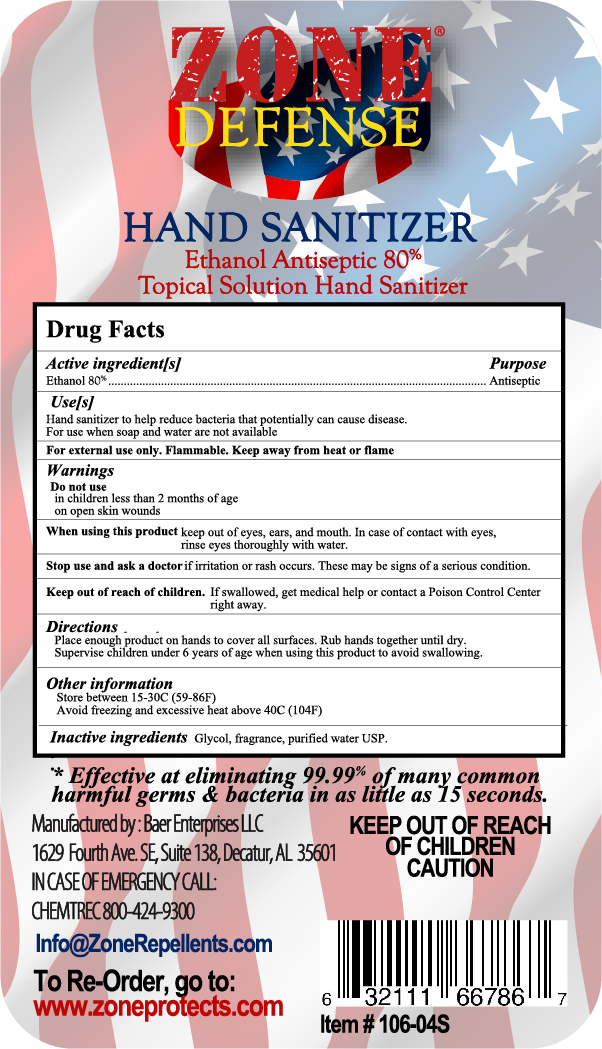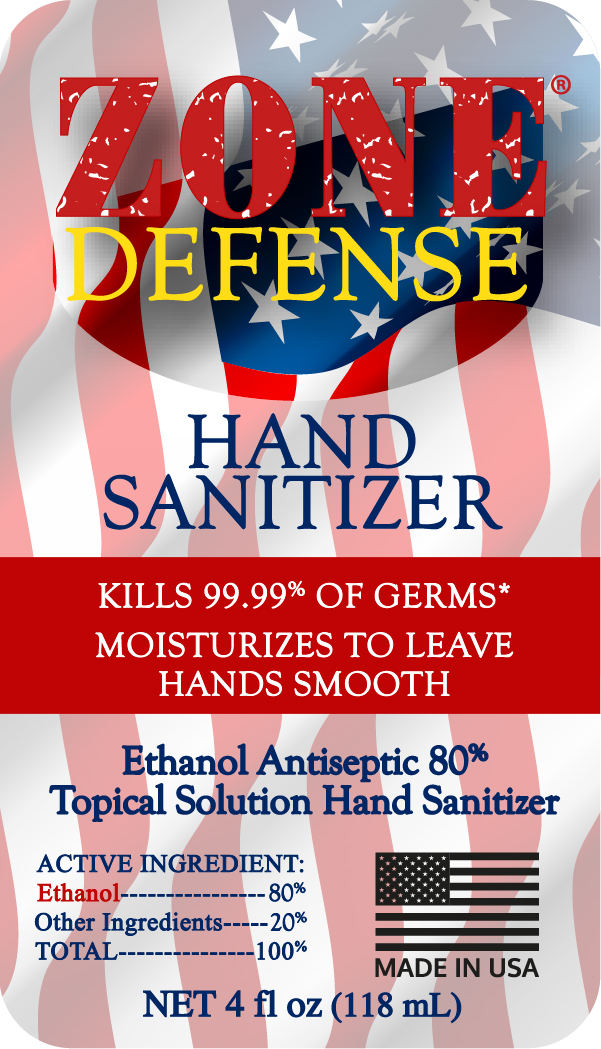 DRUG LABEL: Zone Defense Hand Sanitizer
NDC: 73829-106 | Form: LIQUID
Manufacturer: Baer Enterprises, LLC
Category: otc | Type: HUMAN OTC DRUG LABEL
Date: 20220124

ACTIVE INGREDIENTS: ALCOHOL 94.4 mL/118 mL
INACTIVE INGREDIENTS: POLYETHYLENE GLYCOL 400 4.72 mL/118 mL; WATER 18.87 mL/118 mL; O-ETHYLVANILLIN 0.01 mL/118 mL

1. Alcohol (ethanol) (80%, volume/volume (v/v)) i
2. Glycol (4.0% v/v).
3. Fragrance (0.0% v/v).
4. Sterile distilled water or boiled cold water.

Active Ingredient(s)

Alcohol 80% v/v. Purpose: Antiseptic

Purpose

Antiseptic, Hand Sanitizer

Use

Hand Sanitizer to help reduce bacteria that potentially can cause disease. For use when soap and water are not available.

Warnings

For external use only. Flammable. Keep away from heat or flame

Do not use

- in children less than 2 months of age
- on open skin wounds

When using this product keep out of eyes, ears, and mouth. In case of contact with eyes, rinse eyes thoroughly with water.
Stop use and ask a doctor if irritation or rash occurs. These may be signs of a serious condition.
Keep out of reach of children. If swallowed, get medical help or contact a Poison Control Center right away.

Stop use and ask a doctor if irritation or rash occurs. These may be signs of a serious condition.

Keep out of reach of children. If swallowed, get medical help or contact a Poison Control Center right away.

Directions

- Place enough product on hands to cover all surfaces. Rub hands together until dry.
- Supervise children under 6 years of age when using this product to avoid swallowing.

Other information

- Store between 15-30C (59-86F)
- Avoid freezing and excessive heat above 40C (104F)

Inactive ingredients

glycol, fragrance, purified water USP

Package Label - Principal Display Panel

118 mL NDC: 73829-106-04